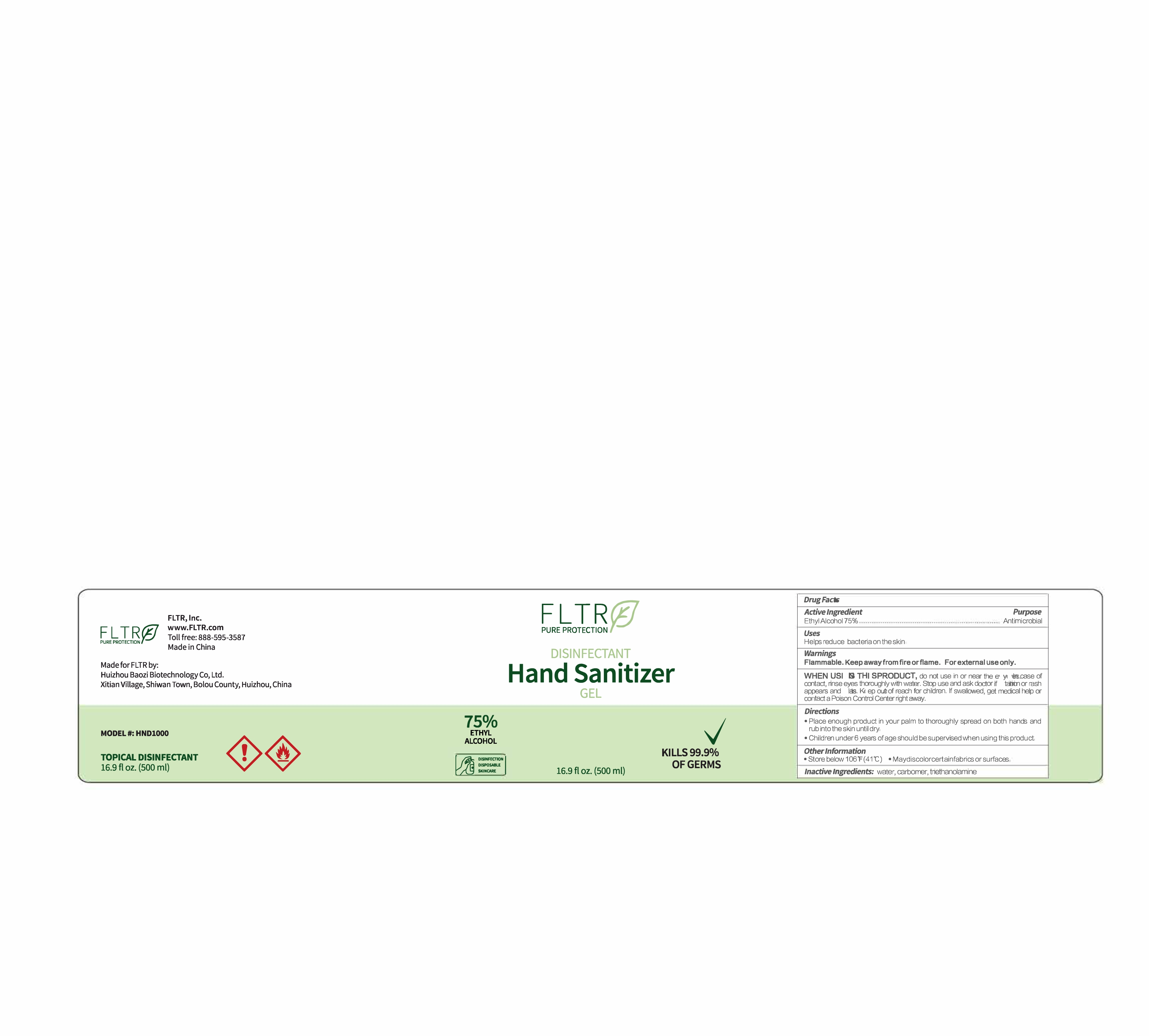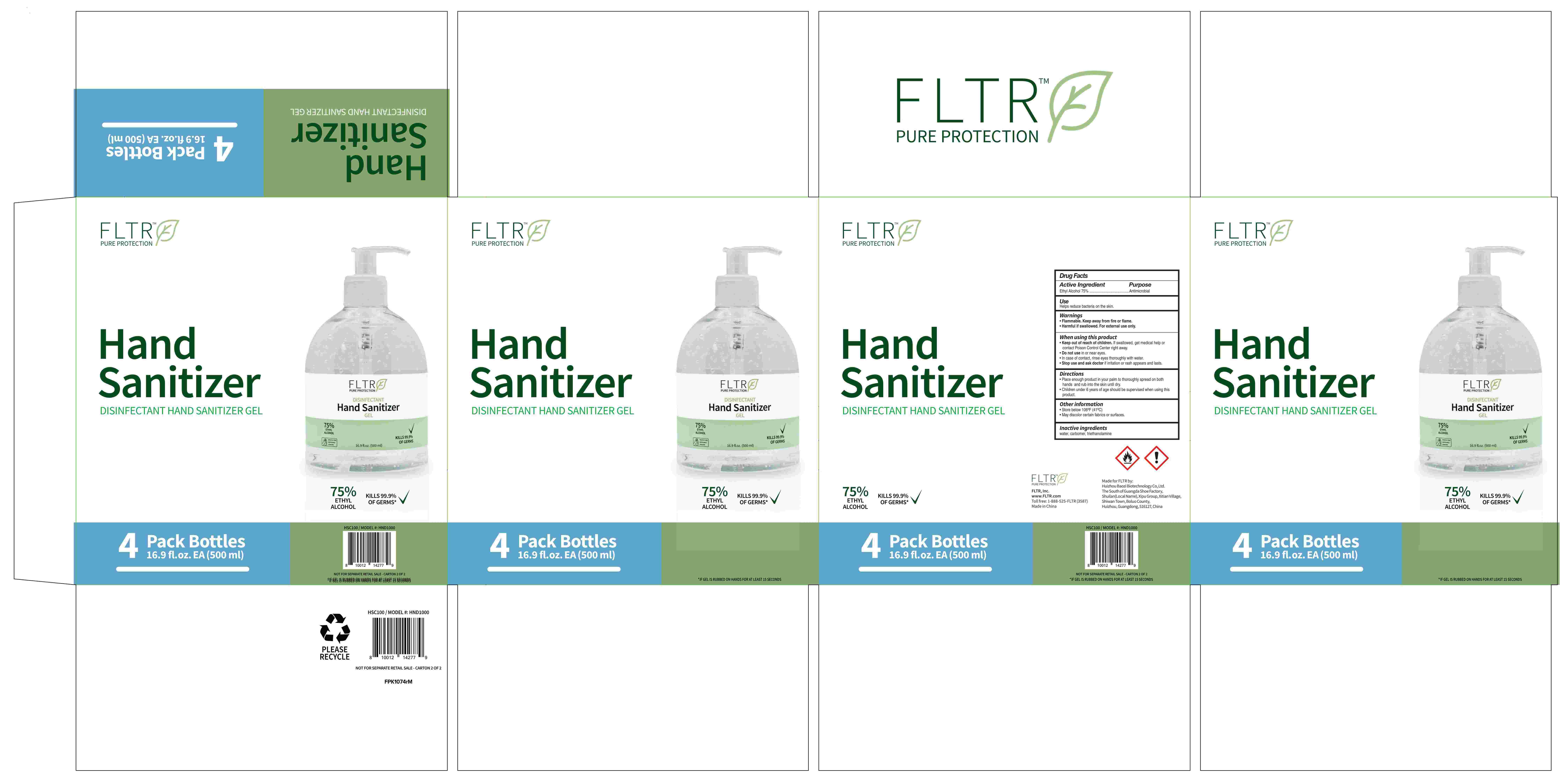 DRUG LABEL: Hand Sanitizer
NDC: 74881-006 | Form: GEL
Manufacturer: Huizhou Baozi Biotechnology Co., Ltd.
Category: otc | Type: HUMAN OTC DRUG LABEL
Date: 20210106

ACTIVE INGREDIENTS: ALCOHOL 75 mL/100 mL
INACTIVE INGREDIENTS: CARBOMER INTERPOLYMER TYPE A (55000 CPS); WATER; TROLAMINE

74881-006
Hand Sanitizer

Active Ingredient

Ethyl Alcohol 75%

Purpose

Antimicrobial

Uses

Helps reduce bacteria on the s k in

Warnings

Flammable Keep awayfromfireorflame. For external use only.

When using this product do not use in or near the eyes

When using this product do not use in or near the eyes. Incase of contact, rinese eyes thoroughly with water, Stop use and ask doctor if irritation or rash appears and lasts, Keep out of reach for children. If swallowed , get medical help or contact a Poison Control Center right away.

stop use and ask a doctor if imitation or rash appears and lasts.

Keep out of reach of children. If swallowed, get medical help or contact a Poison Control Center right away

Directions

Directions: Place enough product in your palm to thoroughly spread on both hands and rub into the skin until dry

Children under 6 years of age should be supervised when using this product

Other information

Store below 106F(41C).May discolor certain fabnics orsurfaces

Inactive ingredients

nactive Ingredients: water, carbomer, triethanolamine

Package Label - Principal Display Panel

HSC100_Retail box_Hand Sanitizer 4PK

74881-006-01